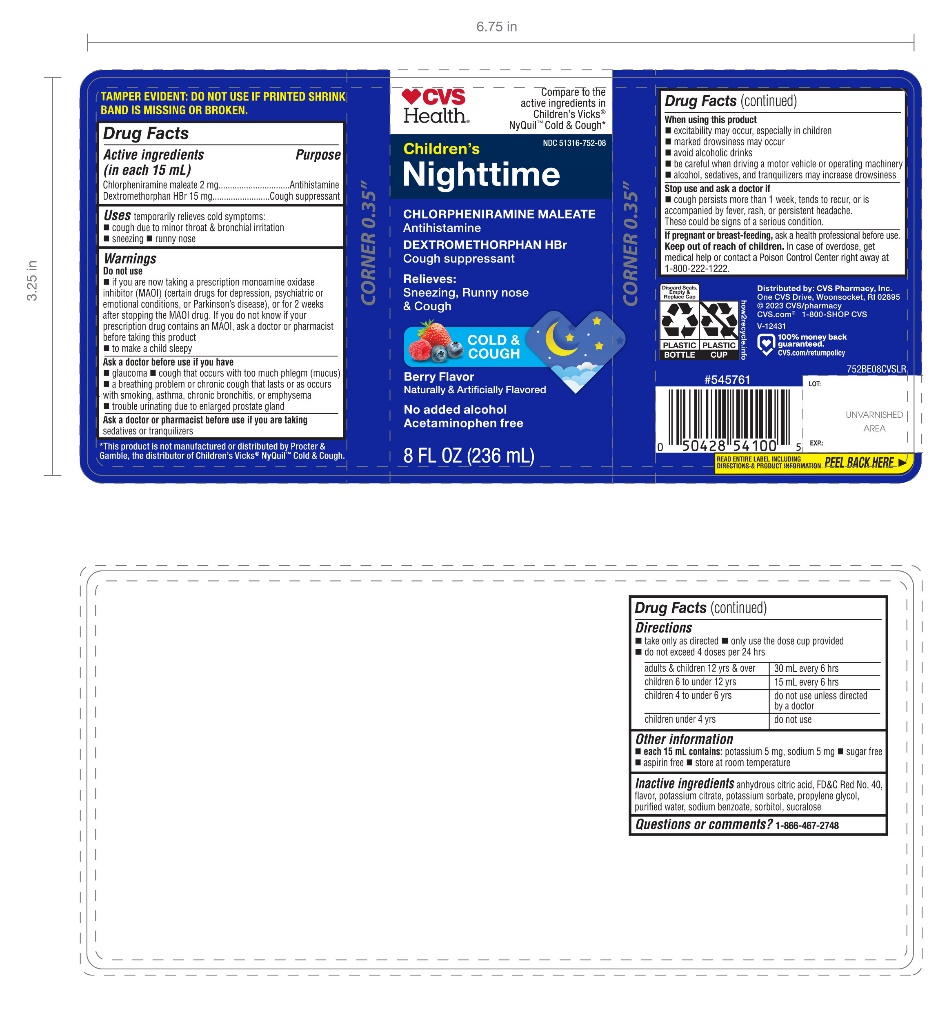 DRUG LABEL: CVS Nighttime Childrens

NDC: 51316-752 | Form: SOLUTION
Manufacturer: CVS PHARMACY
Category: otc | Type: HUMAN OTC DRUG LABEL
Date: 20251210

ACTIVE INGREDIENTS: CHLORPHENIRAMINE MALEATE 2 mg/15 mL; DEXTROMETHORPHAN HYDROBROMIDE 15 mg/15 mL
INACTIVE INGREDIENTS: ANHYDROUS CITRIC ACID; FD&C RED NO. 40; POTASSIUM CITRATE; POTASSIUM SORBATE; PROPYLENE GLYCOL; WATER; SODIUM BENZOATE; SORBITOL; SUCRALOSE

CVS Nighttime Children's Cold & Cough Relief

Drug Facts

ACTIVE INGREDIENT

Active ingredients (in each 15 mL) | Purpose
Chlorpheniramine maleate 2 mg | Antihistamine
Dextromethorphan HBr 15 mg | Cough suppressant

Uses

temporarily relieves cold symptoms:

- cough due to minor throat & bronchial irritation
- sneezing
- runny nose

Warnings

Do not use

- if you are now taking a prescription monoamine oxidase inhibitor (MAOI) (certain drugs for depression, psychiatric or emotional conditions, or Parkinson's disease), or for 2 weeks after stopping the MAOI drug. If you do not know if your prescription drug contains an MAOI, ask a doctor or pharmacist before taking this product.
- to make a child sleepy

Ask a doctor before use if you have

- glaucoma
- cough that occurs with too much phlegm (mucus)
- a breathing problem or chronic cough that lasts or as occurs with smoking, asthma, chronic bronchitis or emphysema
- trouble urinating due to enlarged prostate gland

Ask a doctor or pharmacist before use if you aretaking sedatives or tranquilizers.

When using this product

- excitability may occur, especially in children
- marked drowsiness may occur
- avoid alcoholic drinks
- be careful when driving a motor vehicle or operating machinery
- alcohol, sedatives, & tranquilizers may increase drowsiness

Stop use and ask a doctor if

- cough persists more than 1 week, tends to recur or is accompanied by fever, rash, or persistent headache.

These could be signs of a serious condition.

PREGNANCY OR BREAST FEEDING

If pregnant or breast-feeding, ask a health professional before use.

Keep out of reach of children.In case of overdose, get medical help or contact a Poison Control Center right away at 1-800-222-1222.

Directions

- take only as directed
- do not exceed 4 doses per 24 hrs.
- only use the dose cup provided

adults & children 12 yrs & over | 30 mL every 6 hrs.
children 6 to under 12 yrs | 15 mL every 6 hrs.
children 4 to under 6 yrs | do not use unless directed by a doctor
children under 4 yrs | do not use

Other information

- each 15 mL contains:potassium 5 mg, sodium 5 mg
- sugar free
- aspirin free
- store at room temperature

Inactive ingredients

anhydrous citric acid, FD&C Red No. 40, flavor, potassium citrate, potassium sorbate, propylene glycol, purified water, sodium benzoate, sorbitol, sucrose

Questions or comments?

1-866-467-2748

PRINCIPAL DISPLAY PANEL - 236 ml Bottle Label

Compare to the active ingredients in Children’s Vicks Nyquil™ Cold & Cough*

NDC 51316-752-08

Nighttime

Childrens

Cold & Cough

Chlorpheniramine maleate 2 mg,

Dextromethorphan HBr 15 mg

- Sneezing
- Runny Nose
- Cough

No Added Alcohol, Acetaminophen Free

Berry Flavor

Naturally and Artificially Flavored

8 FL OZ (236 ml)

DISTRIBUTED BY:

TAMPER EVIDENT:Do not use if printed shrink band is missing or broken.

*This product is not manufactured or distributed by Procter & Gamble, the distributor of Children’s Vicks®Nyquil™ Cold & Cough.